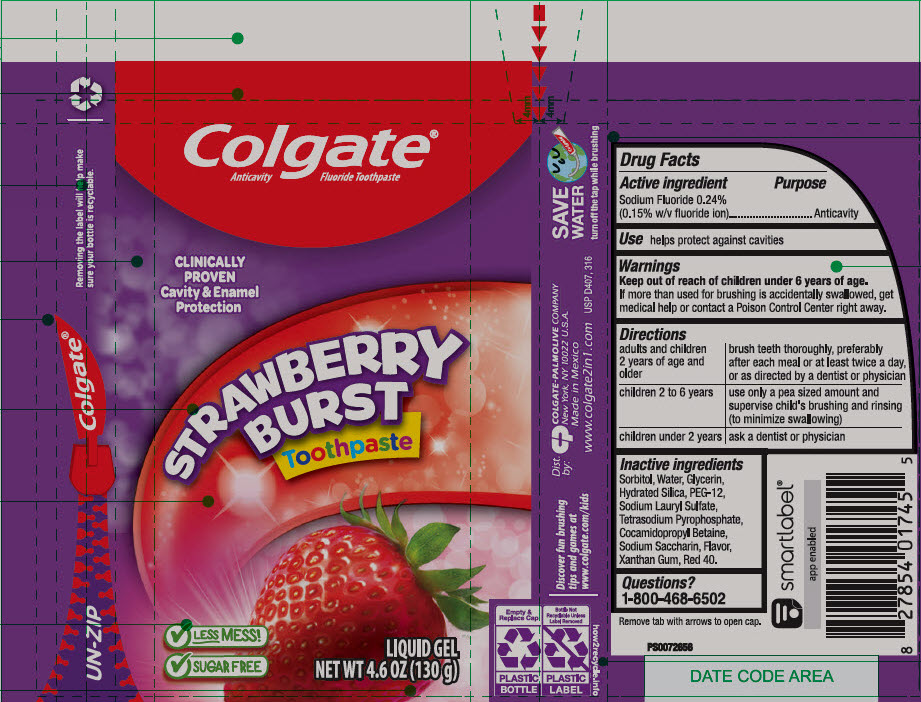 DRUG LABEL: COLGATE 2 IN 1 KIDS SP STRAWBERRY
NDC: 65954-832 | Form: GEL, DENTIFRICE
Manufacturer: Mission Hills, S.A. de C.V.
Category: otc | Type: HUMAN OTC DRUG LABEL
Date: 20241114

ACTIVE INGREDIENTS: SODIUM FLUORIDE 1.1 mg/1 g
INACTIVE INGREDIENTS: SORBITOL 680 mg/1 g; WATER; GLYCERIN; HYDRATED SILICA; POLYETHYLENE GLYCOL 600; SODIUM LAURYL SULFATE; SODIUM PYROPHOSPHATE; COCAMIDOPROPYL BETAINE; SACCHARIN SODIUM; XANTHAN GUM

COLGATE® 2 IN 1 KIDS SP STRAWBERRY

Drug Facts

Active ingredient

Sodium Fluoride 0.24% (0.15% w/v fluoride ion)

Purpose

Anticavity

Use

helps protect against cavities

Warnings

Keep out of reach of children under 6 years of age.

If more than used for brushing is accidentally swallowed, get medical help or contact a Poison Control Center right away.

Directions

adults and children 2 years of age and older | brush teeth thoroughly, preferably after each meal or at least twice a day, or as directed by a dentist or physician
children 2 to 6 years | use only a pea sized amount and supervise child's brushing and rinsing (to minimize swallowing)
children under 2 years | ask a dentist or physician

Inactive ingredients

Sorbitol, Water, Glycerin, Hydrated Silica, PEG-12, Sodium Lauryl Sulfate, Tetrasodium Pyrophosphate, Cocamidopropyl Betaine, Sodium Saccharin, Flavor, Xanthan Gum, Red 40.

Questions?

1-800-468-6502

Dist. by: COLGATE-PALMOLIVE COMPANY
New York, NY 10022 U.S.A.

PRINCIPAL DISPLAY PANEL - 130 g Tube Label

Colgate®
Anticavity Fluoride Toothpaste

CLINICALLY
PROVEN
Cavity & Enamel
Protection

STRAWBERRY
BURST
Toothpaste

✓ LESS MESS!
✓ SUGAR FREE

LIQUID GEL
NET WT 4.6 OZ (130 g)